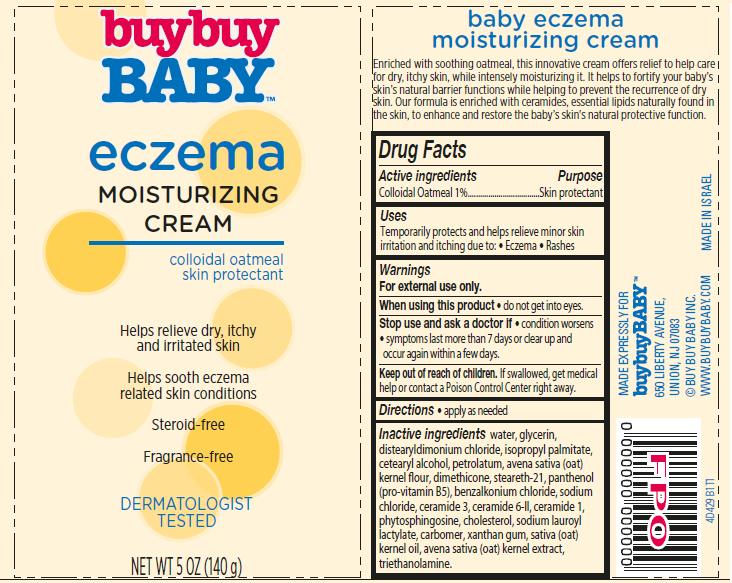 DRUG LABEL: Baby Eczema Moisturizing
NDC: 63940-429 | Form: CREAM
Manufacturer: Harmon Stores Inc.
Category: otc | Type: HUMAN OTC DRUG LABEL
Date: 20140912

ACTIVE INGREDIENTS: OATMEAL 1 g/100 g
INACTIVE INGREDIENTS: WATER; GLYCERIN; DISTEARYLDIMONIUM CHLORIDE; ISOPROPYL PALMITATE; CETOSTEARYL ALCOHOL; PETROLATUM; DIMETHICONE; STEARETH-21; PANTHENOL; BENZALKONIUM CHLORIDE; SODIUM CHLORIDE; CERAMIDE 3; CERAMIDE 6 II; CERAMIDE 1; PHYTOSPHINGOSINE; CHOLESTEROL; SODIUM LAUROYL LACTYLATE; XANTHAN GUM; OAT KERNEL OIL; OAT; TROLAMINE

buybuy Baby™ Eczema Moisturizing Cream

Active ingredient

Colloidal Oatmeal 1%

Purpose

Skin Protectant

Uses

Temporarily protects and helps relieve minor skin irritation and itching due to:

- Eczema
- Rashes

Warnings

For external use only.

When using this product

- do not get into eyes.

Stop use and ask a doctor if

- condition worsens
- symptoms last more than 7 days or clear up and occur again within a few days.

Keep Out of Reach of Children.

If swallowed, get medical help or contact a Poison Control Center right away.

Directions

- apply as needed

Inactive ingredients

water, glycerin, distearyldimonium chloride, isopropyl palmitate, cetearyl alcohol, petrolatum, avena sativa (oat) kernel flour, dimethicone, steareth-21, panthenol (pro-vitamin B5), benzalkonium chloride, sodium chloride, ceramide 3, ceramide 6-II, ceramide 1, phytosphingosine, cholesterol, sodium lauroyl lactylate, carbomer, xanthan gum, sativa (oat) kernel oil, avena sativa (oat) kernel extract, triethanolamine.

Package/Label Principal Display Panel

buybuy
BABY™
eczema
MOISTURIZING
CREAM

colloidal oatmeal
skin protectant

Helps relieve dry, itchy
and irritated skin

Helps sooth eczema
related skin conditions

Steroid-free

Fragrance-free

DERMATOLOGIST
TESTED

NET WT 5 OZ (140 g)

baby eczema
moisturizing cream

Enriched with soothing oatmeal, this innovative cream offers relief to help care
for dry, itchy skin, while intensely moisturizing it. It helps to fortify your baby’s
skin's natural barrier functions while helping to prevent the recurrence of dry
skin. Our formula is enriched with ceramides, essential lipids naturally found in
the skin, to enhance and restore the baby’s skin's natural protective function.

MADE EXPRESSLY FOR
buybuy BABY™
650 Liberty Avenue,
Union, NJ 07083
© BUY BUY BABY INC.
WWW.BUYBUYBABY.COM
MADE IN ISRAEL

Container Label